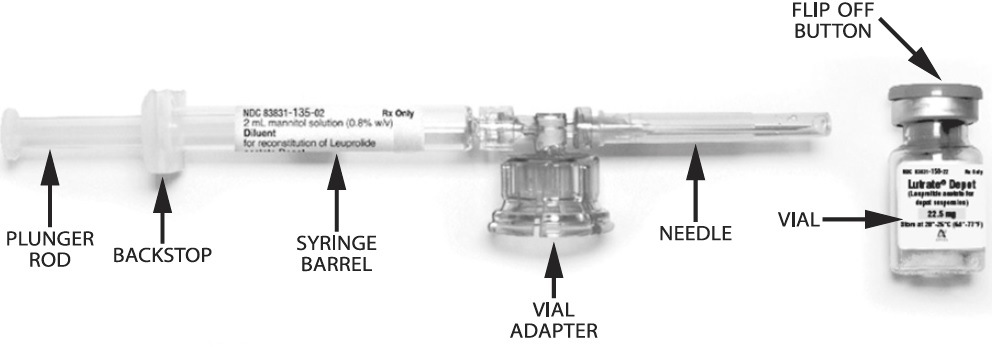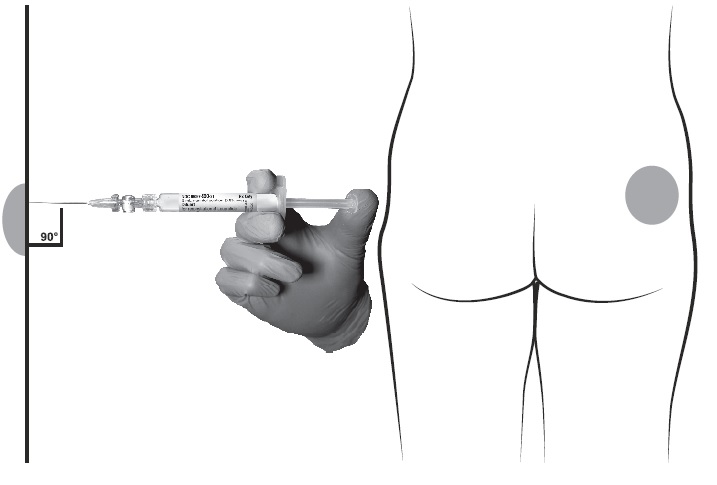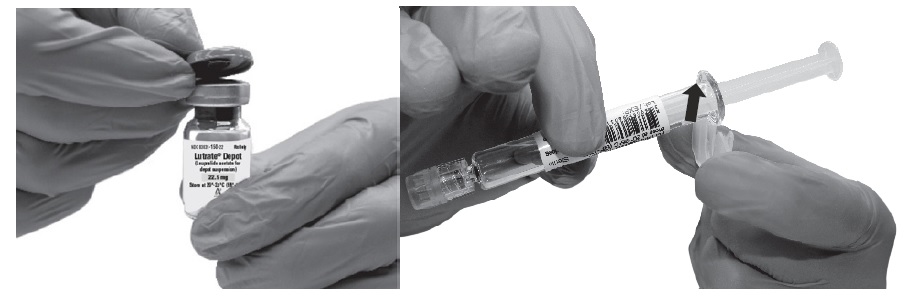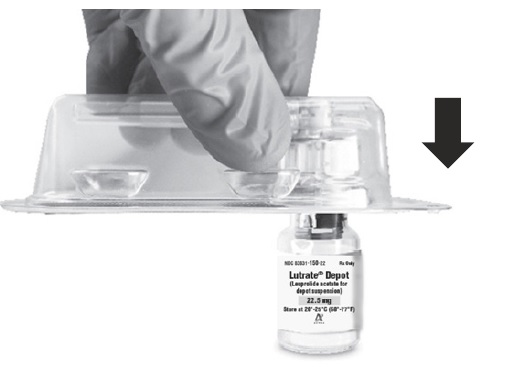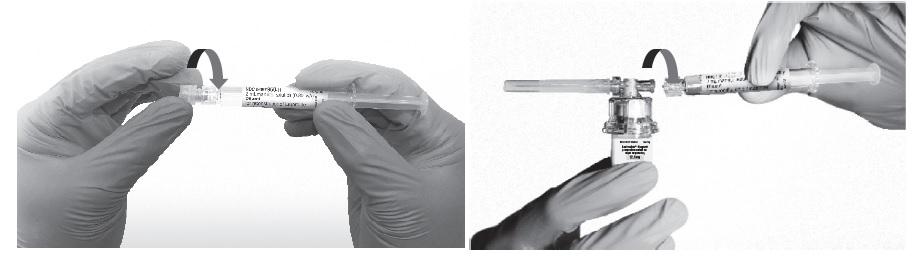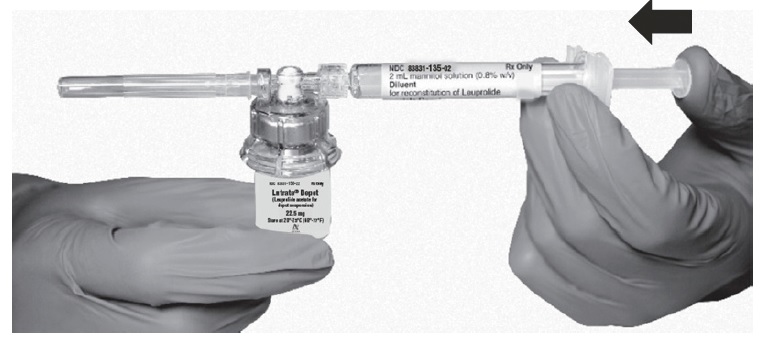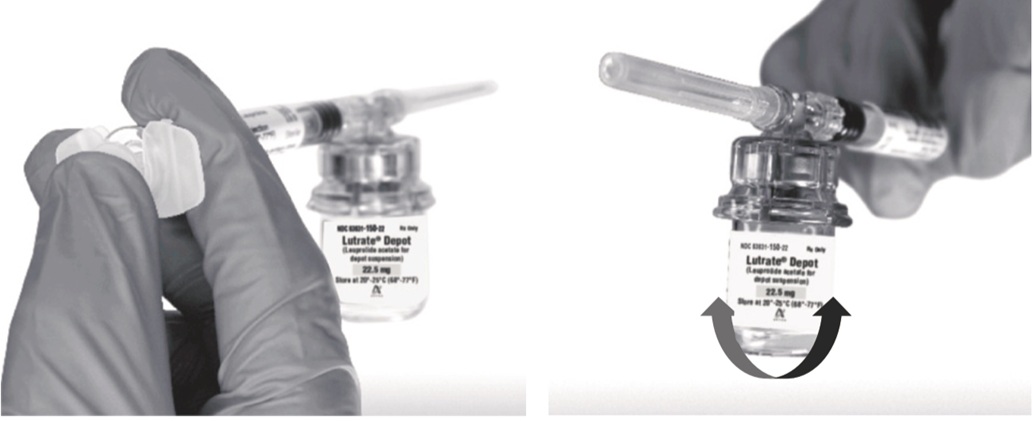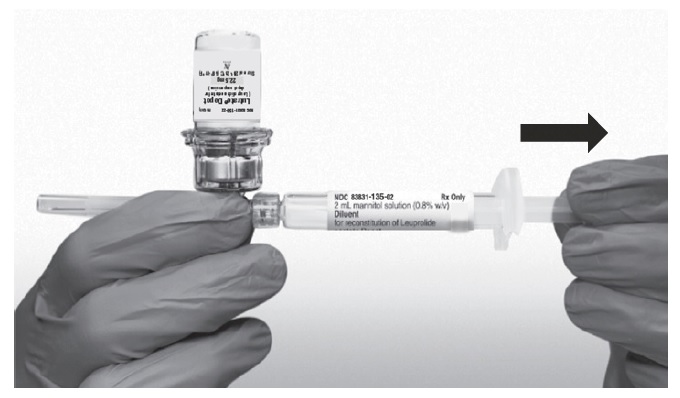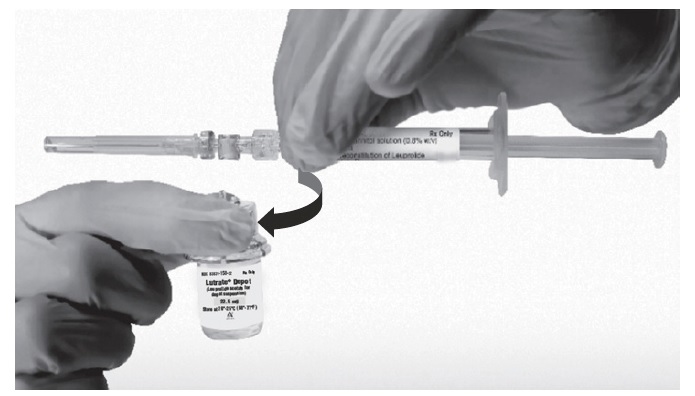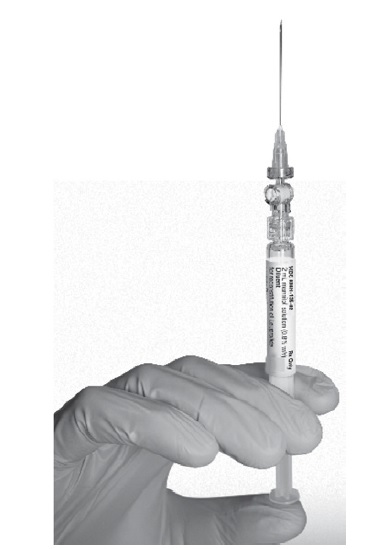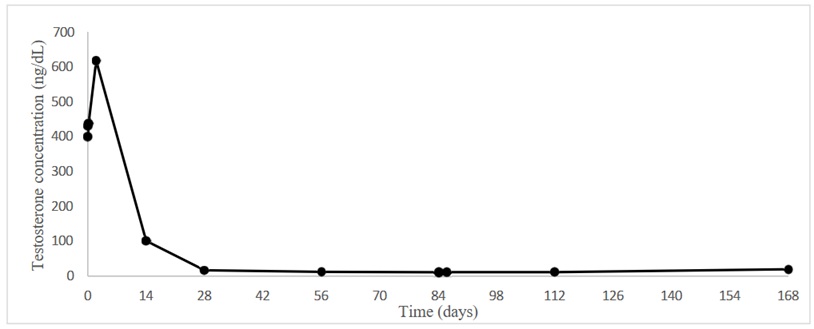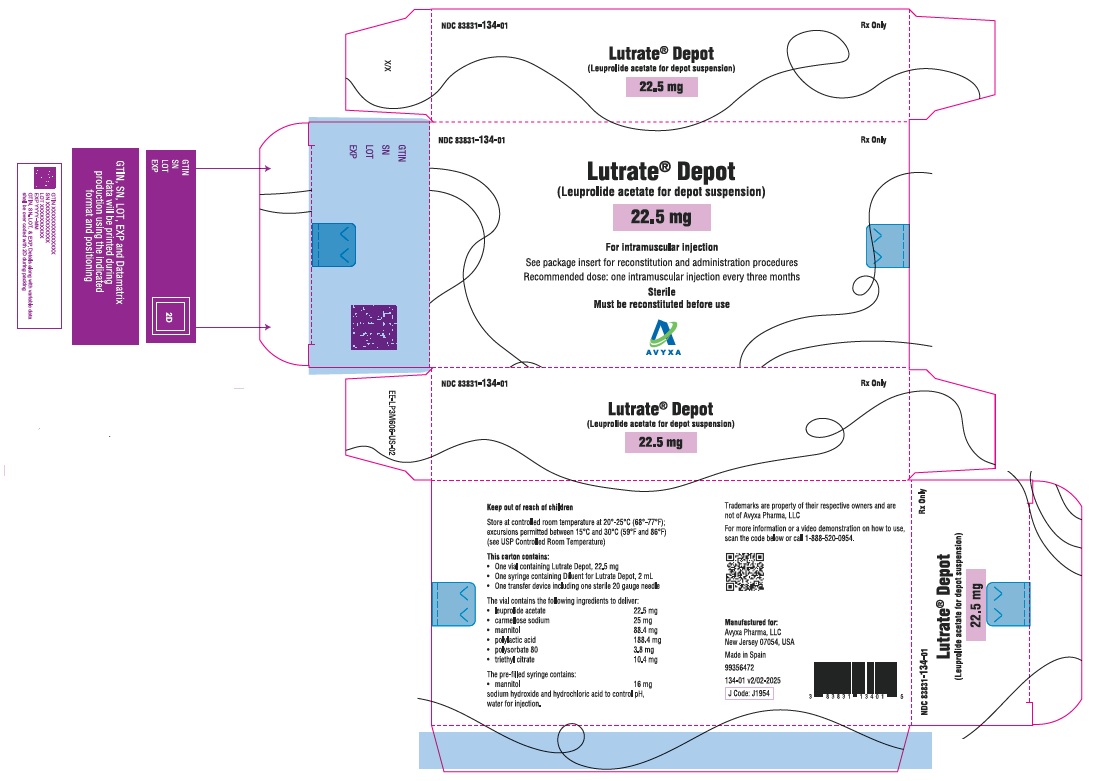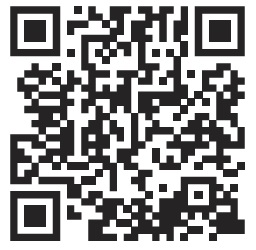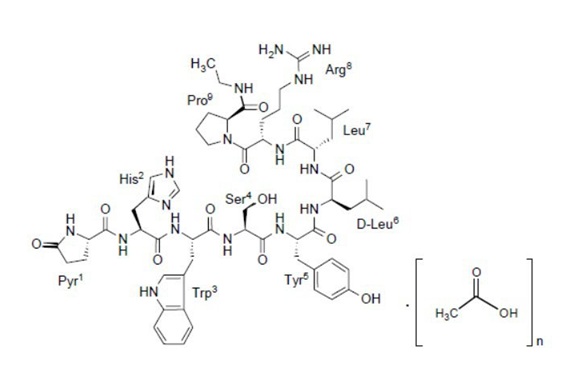 DRUG LABEL: LUTRATE DEPOT
NDC: 83831-134 | Form: KIT | Route: INTRAMUSCULAR
Manufacturer: Avyxa Pharma, LLC
Category: prescription | Type: HUMAN PRESCRIPTION DRUG LABEL
Date: 20250603

ACTIVE INGREDIENTS: LEUPROLIDE ACETATE 22.5 mg/2 mL
INACTIVE INGREDIENTS: CARBOXYMETHYLCELLULOSE SODIUM, UNSPECIFIED 25 mg/2 mL; MANNITOL 88.4 mg/2 mL; POLYLACTIDE 188.4 mg/2 mL; POLYSORBATE 80 3.8 mg/2 mL; TRIETHYL CITRATE 10.4 mg/2 mL; MANNITOL

HIGHLIGHTS OF PRESCRIBING INFORMATION

These highlights do not include all the information needed to use LUTRATE DEPOT safely and effectively. See full prescribing information for LUTRATE DEPOT.
LUTRATE® DEPOT (leuprolide acetate), for depot suspension
Initial U.S. Approval: 2018

RECENT MAJOR CHANGES

Warnings and Precautions (5.6) 11/2024

1 INDICATIONS AND USAGE

LUTRATE DEPOT is a gonadotropin-releasing hormone (GnRH) agonist indicated for:

- Treatment of advanced prostate cancer. (1)

2 DOSAGE AND ADMINISTRATION

Due to different release characteristics, the dosage strengths are not additive and must be selected based upon the desired dosing schedule (2).

- LUTRATE DEPOT 22.5 mg for 3 months administration, given as a single intramuscular injection every 12 weeks. (2.1)

3 DOSAGE FORMS AND STRENGTHS

For Injection: 22.5 mg of leuprolide acetate in a single dose vial as a kit with a prefilled syringe containing diluent and a MIXJECT transfer device. (3)

4 CONTRAINDICATIONS

- Hypersensitivity to GnRH, GnRH agonist or any of the excipients in LUTRATE DEPOT. (4).

5 WARNINGS AND PRECAUTIONS

- Tumor Flare: Increased serum testosterone (~50% above baseline) during first week of treatment; monitor serum testosterone and PSA. (5.7)
  - Transient worsening of symptoms, or additional signs and symptoms of prostate cancer during the first few weeks of treatment. (5.1)
  - Patients may experience a temporary increase in bone pain which can be managed symptomatically. (5.1)
  - Ureteral obstruction and spinal cord compression have been reported with GnRH agonists, which may contribute to paralysis with or without fatal complications. (5.1)
- Metabolic Syndrome: The use of GnRH agonists may lead to an increased risk of metabolic changes such as hyperglycemia, diabetes, hyperlipidemia, and non-alcoholic fatty liver disease. Monitor for signs and symptoms of metabolic syndrome including lipids, blood glucose level and/or HbA1c and manage according to current treatment guidelines. (5.2)
- Cardiovascular Diseases: Increased risk of myocardial infarction, sudden cardiac death and stroke has been reported in association with use of GnRH analogs in men. Monitor for cardiovascular disease and manage according to current clinical practice. (5.3)
- Effect on QT/QTc Interval: Androgen deprivation therapy may prolong QT interval. Consider risks and benefits. (5.4)
- Convulsions have been observed in patients with or without a history of predisposing factors. Manage convulsions according to the current clinical practice. (5.5)
- Severe Cutaneous Adverse Reactions (SCARs), including Stevens-Johnson syndrome/toxic epidermal necrolysis (SJS/TEN), may occur in patients treated with LUTRATE DEPOT. Interrupt LUTRATE DEPOT if signs or symptoms of SCARs develop. Permanently discontinue if SCARs are confirmed. (5.6)
- Monitor serum levels of testosterone following injection of LUTRATE DEPOT 22.5 mg for 3-month administration. (5.7)
- Embryo-Fetal Toxicity: LUTRATE DEPOT may cause fetal harm. (5.8, 8.1)

6 ADVERSE REACTIONS

Most common adverse reactions (incidence > 10%) are hot flushes, upper respiratory infection, fatigue, diarrhea, pollakiuria, arthralgia, and injection site pain (6).

As with other GnRH agonist, other adverse reactions, including decreased bone density and rare cases of pituitary apoplexy may occur. (6)

To report SUSPECTED ADVERSE REACTIONS, contact Avyxa Pharma, LLC at 1-888-520-0954 or FDA at 1-800-FDA-1088 or www.fda.gov/medwatch.

8 USE IN SPECIFIC POPULATIONS

- Females and males of reproductive potential: LUTRATE DEPOT may impair fertility. Counsel patients on pregnancy planning and prevention. (8.3)
- Pediatric: The use of LUTRATE DEPOT formulations are not indicated for use in children. (8.4)
- Geriatric: This label reflects clinical trials for LUTRATE DEPOT in prostate cancer in which the majority of the subjects studied were at least 65 years of age. (8.5)

FULL PRESCRIBING INFORMATION

1 INDICATIONS AND USAGE

LUTRATE DEPOT 22.5 mg for 3-month administration (leuprolide acetate) is indicated for treatment of advanced prostate cancer.

2 DOSAGE AND ADMINISTRATION

2.1 LUTRATE DEPOT 22.5 mg for 3-Month Administration

LUTRATE DEPOT must be administered under the supervision of a physician.

In patients treated with GnRH analogues for prostate cancer, treatment is usually continued upon development of metastatic castration-resistant prostate cancer.

Table 1. LUTRATE DEPOT Recommended Dosing
Dosage | 22.5 mg for 3-Month Administration
Recommended Dose | 1 injection every 12 weeks

The recommended dose of LUTRATE DEPOT 22.5 mg for 3-month administration is one injection every 12 weeks. Do not use concurrently a fractional dose, or a combination of doses of this or any depot formulation due to different release characteristics.

Incorporated in a depot formulation, the lyophilized microspheres must be reconstituted and administered every 12 weeks as a single intramuscular injection.

2.2 Reconstitution Instructions for LUTRATE DEPOT

- Reconstitute and administer the lyophilized microspheres as a single intramuscular injection.
- The suspension should be administered immediately after reconstitution.
- As with other drugs administered by intramuscular injection, the injection site should be alternated periodically.
- Visually inspect LUTRATE DEPOT powder (white to off-white powder). DO NOT USE the vial if clumping or caking is evident. A thin layer of powder on the wall of the vial is considered normal prior to mixing with the diluent. The diluent contained in the prefilled syringe should appear clear and colorless.
- Use ONLY the provided diluent for reconstitution of LUTRATE DEPOT. DO NOT use other diluents.
- The reconstituted product is a suspension of milky, white color appearance.

LUTRATE DEPOT is packaged in a commercial kit. Each kit contains:

- One vial containing 22.5 mg of leuprolide acetate as lyophilized microspheres.
- One prefilled syringe containing 2 mL of mannitol for injection.
- One MIXJECT transfer device including one needle.

Please read the instructions completely before you begin.

MIXJECT Preparation

Wash your hands with soap and hot water and put on gloves^1 immediately prior to preparing the injection. Place the tray on a clean, flat surface that is covered with a sterile pad or cloth. Remove the MIXJECT device, the backstop, the prefilled syringe containing the solvent for reconstitution and the LUTRATE DEPOT vial.

Remove the Flip-Off button from the top of the vial, revealing the rubber stopper. Place the vial in a standing upright position on the prepared surface. Disinfect the rubber stopper with the alcohol wipe. Discard the alcohol wipe and allow the stopper to dry. Insert the backstop to the flange of the syringe until you feel it snap in place. Proceed to MIXJECT Activation.

MIXJECT Activation

1. Peel the cover away from the blister pack containing the vial adapter (MIXJECT). Do not remove the vial adapter from the blister pack. Place the blister pack containing the vial adapter firmly on the vial top, piercing the vial. Push down gently until you feel it snap in place.
2. Remove the cap from the syringe barrel and then, remove the blister pack from the vial adapter. Connect the syringe to the vial adapter by screwing it clockwise into the opening on the side of the vial adapter. Be sure to gently twist the syringe until it stops turning to ensure a tight connection.
3. While holding the vial, place your thumb on the plunger rod and push the plunger rod in all the way to transfer the diluent from the pre-filled syringe into the vial. Do not release the plunger rod.
4. Keeping the plunger rod depressed, gently swirl the vial for approximately one minute until a uniform milky-white suspension is obtained. This will ensure complete mixing of LUTRATE DEPOT and the sterile mannitol solution diluent. The suspension will now have a milky appearance. In order to avoid separation of the suspension, proceed to the next steps without delay.
5. Invert the MIXJECT system so that the vial is at the top. Grasp the MIXJECT system firmly by the syringe and pull back the plunger rod slowly to draw the reconstituted LUTRATE DEPOT into the syringe.
  Return the vial to its upright position, and disconnect the vial adapter from the MIXJECT syringe assembly by grabbing firmly the syringe and turning the plastic cap of the vial adapter clockwise. Grasp only the plastic cap when removing.
6. Keep the syringe UPRIGHT. With the opposite hand pull the needle cap upward. Advance the plunger to expel the air from the syringe. The syringe containing LUTRATE DEPOT is now ready for administration. The suspension should be administered immediately after reconstitution.
7. After cleaning the injection site with an alcohol swab, administer the intramuscular injection by inserting the needle at a 90 degree angle into the gluteal area, anterior thigh, or deltoid; injection sites should be alternated (see Figure).
  NOTE: If a blood vessel is accidentally penetrated, aspirated blood will be visible just below the luer lock. If blood is present, remove the needle immediately. Do not inject the medication.
8. Inject the entire contents of the syringe intramuscularly.
9. Withdraw the needle. Once the syringe has been withdrawn, immediately discard the needle into a suitable sharps container. Dispose the syringe according to local regulations/procedures.

3 DOSAGE FORMS AND STRENGTHS

LUTRATE DEPOT

For Injection: 22.5 mg of leuprolide acetate for 3-month administration as lyophilized microspheres in a single dose vial as a kit with a prefilled syringe containing 2mL 0.8% mannitol solution and a MIXJECT transfer device for a single dose injection.

4 CONTRAINDICATIONS

LUTRATE DEPOT is contraindicated in:

- Hypersensitivity
  LUTRATE DEPOT is contraindicated in individuals with known hypersensitivity to GnRH agonists or any of the excipients in LUTRATE DEPOT. Reports of anaphylactic reactions to GnRH agonists have been reported in the medical literature.

5 WARNINGS AND PRECAUTIONS

5.1 Tumor Flare

Initially, LUTRATE DEPOT, like other GnRH agonists, causes increases in serum levels of testosterone to approximately 50% above baseline during the first weeks of treatment. Ureteral obstruction and spinal cord compression have been observed, which may contribute to paralysis with or without fatal complications. Transient worsening of symptoms may develop. Patients may experience a temporary increase in bone pain, which can be managed symptomatically.

Patients with metastatic vertebral lesions and/or with urinary tract obstruction should be closely observed during the first few weeks of therapy.

5.2 Metabolic Syndrome

The use of GnRH agonists may lead to metabolic changes such as hyperglycemia, diabetes mellitus, and hyperlipidemia. Non-alcoholic fatty liver disease, including cirrhosis, occurred in the post-marketing setting. Hyperglycemia may represent new-onset diabetes mellitus or worsening of glycemic control in patients with pre-existing diabetes. Monitor for changes in serum lipids, blood glucose and/or glycosylated hemoglobin (HbA1c) in patients receiving a GnRH agonist, and manage according to current treatment guidelines.

5.3 Cardiovascular Diseases

Increased risk of developing myocardial infarction, sudden cardiac death and stroke has been reported in association with use of GnRH agonists in men. The risk appears low based on the reported odds ratios, and should be evaluated carefully along with cardiovascular risk factors when determining a treatment for patients with prostate cancer. Patients receiving a GnRH agonist should be monitored for symptoms and signs suggestive of development of cardiovascular disease and be managed according to current clinical practice.

5.4 Effect on QT/QTc Interval

Androgen deprivation therapy may prolong the QT/QTc interval. Providers should consider whether the benefits of androgen deprivation therapy outweigh the potential risks in patients with congenital long QT syndrome, congestive heart failure, frequent electrolyte abnormalities, and in patients taking drugs known to prolong the QT interval. Electrolyte abnormalities should be corrected. Consider periodic monitoring of electrocardiograms and electrolytes.

5.5 Convulsions

Postmarketing reports of convulsions have been observed in patients on leuprolide acetate therapy. These included patients with a history of seizures, epilepsy, cerebrovascular disorders, central nervous system anomalies or tumors, and in patients on concomitant medications that have been associated with convulsions such as bupropion and SSRIs. Convulsions have also been reported in patients in the absence of any of the conditions mentioned above. Patients receiving a GnRH agonist who experience convulsion should be managed according to current clinical practice.

5.6 Severe Cutaneous Adverse Reactions

Severe cutaneous adverse reactions (SCARs), including Stevens-Johnson syndrome/toxic epidermal necrolysis (SJS/TEN), drug reaction with eosinophilia and systemic symptoms (DRESS), and acute generalized exanthematous pustulosis (AGEP), may occur in patients receiving LUTRATE DEPOT; including cases with visceral involvement and/or requiring skin grafts [see Adverse Reactions (6.2)].

Monitor patients for the development of SCARs. Advise patients of the signs and symptoms of SCARs (e.g., a prodrome of fever, flu-like symptoms, mucosal lesions, progressive skin rash, or lymphadenopathy).

If a SCAR is suspected, interrupt LUTRATE DEPOT until the etiology of the reaction has been determined. Consultation with a dermatologist is recommended. If a SCAR is confirmed, or for other grade 4 skin reactions, permanently discontinue LUTRATE DEPOT.

5.7 Laboratory Tests

Monitor serum levels of testosterone following injection of LUTRATE DEPOT 22.5 mg for 3-month administration. In the majority of patients, testosterone levels increased above baseline during the first week, and then declined thereafter to castrate levels (< 50 ng/dL) within four weeks. [see Clinical Studies (14) and Adverse Reactions (6)].

5.8 Embryo-Fetal Toxicity

Based on findings in animal studies, LUTRATE DEPOT may cause fetal harm when administered to a pregnant woman. In animal developmental and reproductive toxicology studies, administration of the monthly formulation of leuprolide acetate on day 6 of pregnancy (sustained exposure was expected throughout the period of organogenesis) caused adverse embryo-fetal toxicity in animals at doses less than the human dose, based on body surface area, using an estimated daily dose. Advise pregnant patients and females of reproductive potential of the potential risk to the fetus [see Use in Specific Populations (8.1)].

6 ADVERSE REACTIONS

The following is discussed in more detail in other sections of the labeling:

- Tumor Flare [see Warnings and Precautions (5.1)]
- Metabolic Syndrome [see Warnings and Precautions (5.2)]
- Cardiovascular Disease [see Warnings and Precautions (5.3)]
- Effect on QT/QTc Interval [see Warnings and Precautions (5.4)]
- Convulsions [see Warnings and Precautions (5.5)]
- Severe Cutaneous Adverse Reactions [see Warnings and Precautions (5.6)]

6.1 Clinical Trials Experience

Because clinical trials are conducted under widely varying conditions, adverse reaction rates observed in the clinical trials of a drug cannot be directly compared to rates in the clinical trials of another drug and may not reflect the rates observed in practice.

LUTRATE DEPOT 22.5 mg for 3-Month Administration

In a clinical trial of LUTRATE DEPOT 22.5 mg for 3-month administration, patients were treated for 24 weeks with 157/163 receiving two injections. The table includes adverse reactions were reported in 5% or more of the patients during the treatment period as well as the incidence of these adverse reaction that were considered, by the treating physician, to be at least possibly related to LUTRATE DEPOT. Grade 3-4 adverse reactions reported as treatment-emergent in 13% of patients and treatment-related 4% of patients.

Table 2. Adverse Reactions Reported in ≥ 5% of Patients
LUTRATE DEPOT 22.5 mg for 3-Month Administration
N = 163 (%)
 | Grade 1-4
 | Treatment-Emergent | Treatment-Related
Hot Flush/Flushing^1 | 128 (79) | 127 (78)
Upper Respiratory Infection^2 | 28 (17) | 0
Fatigue/Asthenia | 24 (15) | 22 (13)
Diarrhea | 21 (13) | 2 (1)
Pollakiuria | 20 (12) | 3 (2)
Arthralgia/Arthritis | 18 (11) | 2 (1)
Injection Site Pain/Discomfort | 18 (11) | 15 (9)
Constipation | 15 (9) | 1 (0.6)
Extremity Pain | 14 (9) | 0
Nausea | 14 (9) | 4 (2)
Nocturia | 14 (9) | 3 (2)
Abdominal Pain/Discomfort | 13 (8) | 1 (0.6)
Urinary Tract Pain | 13 (8) | 2 (1)
Dizziness | 12 (7) | 2 (1)
Headache/Sinus Headache | 12 (7) | 1 (0.6)
Urinary Tract Infection | 12 (7) | 0
Bone Pain | 11 (7) | 4 (2)
Back Pain | 10 (6) | 1 (0.6)
Hypertension/Blood Pressure Increased | 10 (6) | 0
Pruritus/Generalized Pruritus | 9 (6) | 3 (2)
CTCAE v.3
^1 Includes cold sweat, flushing, hot flush, hyperhidrosis, and night sweats
^2Includes influenza, influenza-like illness, nasal congestion, nasopharyngitis, rhinorrhea, upper respiratory tract infection and congestion

In the same study, erectile dysfunction and testicular atrophy were reported in patients on LUTRATE DEPOT 22.5 mg.

Laboratory abnormalities

During the treatment period, at least a one grade change in laboratory values was seen (>10%) in the following: anemia, increased triglyceride, hyperglycemia, increased cholesterol, increased creatine kinase, leukopenia, increased AST, increased creatinine, and increased ALT.

6.2 Post-marketing Experience

The following adverse reactions have been identified during post approval use of gonadotropin-releasing hormone agonists. Because these reactions are reported voluntarily from a population of uncertain size, it is not always possible to reliably estimate their frequency or establish a causal relationship to drug exposure.

Mood swings, including depression, have been reported. There have been very rare reports of suicidal ideation and attempt. Many, but not all, of these patients had a history of depression or other psychiatric illness. Patients should be counseled on the possibility of development or worsening of depression during treatment with LUTRATE DEPOT.

Symptoms consistent with an anaphylactoid or asthmatic process have been rarely (incidence rate of about 0.002%) reported. Rash, urticaria, and photosensitivity reactions have also been reported.

Pituitary apoplexy: During postmarketing surveillance, rare cases of pituitary apoplexy (a clinical syndrome secondary to infarction of the pituitary gland) have been reported after the administration of gonadotropin-releasing hormone agonists. In a majority of these cases, a pituitary adenoma was diagnosed with a majority of pituitary apoplexy cases occurring within 2 weeks of the first dose, and some within the first hour. In these cases, pituitary apoplexy has presented as sudden headache, vomiting, visual changes, ophthalmoplegia, altered mental status, and sometimes cardiovascular collapse. Immediate medical attention has been required.

Localized reactions including induration and abscess have been reported at the site of injection.

Symptoms consistent with fibromyalgia (e.g., joint and muscle pain, headaches, sleep disorders, gastrointestinal distress, and shortness of breath) have been reported individually and collectively.

Changes in Bone Density: Decreased bone density has been reported in the medical literature in men who have had orchiectomy or who have been treated with a GnRH agonist analog. In a clinical trial, 25 men with prostate cancer, 12 of whom had been treated previously with leuprolide acetate for at least six months, underwent bone density studies as a result of pain. The leuprolide acetate-treated group had lower bone density scores than the nontreated control group. It can be anticipated that long periods of medical castration in men will have effects on bone density.

Immune Disorders: Anaphylaxis

Psychiatric Disorders: Depression

Cardiovascular System - hypotension, myocardial infarction, pulmonary embolism

Respiratory, Thoracic and Mediastinal disorder - Pneumonitis, interstitial lung disease

Hepato-biliary disorder - serious drug-induced liver injury, non-alcoholic fatty liver disease

Skin reactions – rash, urticaria, photosensitivity, erythema multiforme, bullous dermatitis, exfoliative dermatitis, DRESS, SJS/TEN, and AGEP

Blood and Lymphatic System - decreased WBC

Central/Peripheral Nervous System - convulsion, peripheral neuropathy, spinal fracture/paralysis

Endocrine System - diabetes mellitus

Musculoskeletal System - tenosynovitis-like symptoms

Urogenital System - prostate pain

7 DRUG INTERACTIONS

No pharmacokinetic-based drug-drug interaction studies have been conducted with LUTRATE DEPOT.

7.1 Drug/Laboratory Test Interactions

Administration of LUTRATE DEPOT in therapeutic doses results in suppression of the pituitary-gonadal system. Normal function is usually restored within three months after treatment is discontinued. Due to the suppression of the pituitary-gonadal system by LUTRATE DEPOT, diagnostic tests of pituitary gonadotropic and gonadal functions conducted during treatment and up to three months after discontinuation of LUTRATE DEPOT may be affected.

8 USE IN SPECIFIC POPULATIONS

8.1 Pregnancy

Risk summary

Based on findings in animal studies and mechanism of action, LUTRATE DEPOT may cause fetal harm when administered to a pregnant woman [see Clinical Pharmacology (12.1)]. There are no available data in pregnant women to inform the drug-associated risk. In animal developmental and reproductive toxicology studies, administration of a monthly formulation of leuprolide acetate on day 6 of pregnancy (sustained exposure was expected throughout the period of organogenesis) caused adverse embryo-fetal toxicity in animals at doses less than the human dose based on body surface area using an estimated daily dose (see data). Advise pregnant patients and females of reproductive potential of the potential risk to the fetus.

Animal Data

Major fetal malformations were observed in developmental and reproductive toxicology studies in rabbits after a single administration of the monthly formulation of leuprolide acetate on day 6 of pregnancy at doses of 0.00024, 0.0024, and 0.024 mg/kg (approximately 1/1600 to 1/16 the human dose based on body surface area using an estimated daily dose in animals and humans). Since a depot formulation was utilized in the study, a sustained exposure to leuprolide acetate was expected throughout the period of organogenesis and to the end of gestation. Similar studies in rats did not demonstrate an increase in fetal malformations, however, there was increased fetal mortality and decreased fetal weights with the two higher doses of the monthly formulation of leuprolide acetate in rabbits and with the highest dose (0.024 mg/kg) in rats.

8.2 Lactation

The safety and efficacy of LUTRATE DEPOT have not been established in females. There is no information regarding the presence of LUTRATE DEPOT in human milk, the effects on the breastfed child, or the effects on milk production. Because many drugs are excreted in human milk and because of the potential for serious adverse reactions in a breastfed child from LUTRATE DEPOT, a decision should be made to discontinue breastfeeding or discontinue the drug, taking into account the importance of the drug to the mother.

8.3 Females and Males of Reproductive Potential

Infertility

Males

Based on findings in animals and mechanism of action, LUTRATE DEPOT may impair fertility in males of reproductive potential [see Nonclinical Toxicology (13.1)].

8.4 Pediatric Use

The safety and effectiveness of LUTRATE DEPOT in pediatric patients have not been established.

8.5 Geriatric Use

In the clinical trials for LUTRATE DEPOT in prostate cancer 74% of the patients studied were at least 65 years of age. Hot flushes occurred with equal frequency in those less than or at least 65 years of age.

10 OVERDOSAGE

There is no experience of overdosage in clinical trials. In rats, a single subcutaneous dose of 100 mg/kg (approximately 4,000 times the estimated daily human dose based on body surface area), resulted in dyspnea, decreased activity, and excessive scratching.

In early clinical trials with daily subcutaneous leuprolide acetate, doses as high as 20 mg/day for up two years caused no adverse effects differing from those observed with the 1 mg/day dose.

11 DESCRIPTION

Leuprolide acetate is a synthetic nonapeptide analog of naturally occurring gonadotropin-releasing hormone (GnRH). The analog possesses greater potency than the natural hormone. The chemical name is 5-oxo-L-prolyl-L-histidyl-L-tryptophyl-L-seryl-L-tyrosyl-D-leucyl-L-leucyl-L-arginyl-N-ethyl-L-prolinamide acetate (salt) with the following structural formula:

Where: n=1 or 2

Leuprolide acetate has a molecular weight of 1209.41 as "free base”. Leuprolide is freely soluble in water.

LUTRATE DEPOT 22.5 mg for 3-month administration is available in a vial containing white to off white sterile lyophilized microspheres together with the corresponding sterile reconstitution diluent in a pre-filled syringe. When LUTRATE DEPOT and the diluent are mixed together they become a suspension intended as an intramuscular injection to be given ONCE EVERY 12 WEEKS as a single dose.

Each vial of LUTRATE DEPOT 22.5 mg for 3-month administration delivers leuprolide acetate (22.5 mg), polylactic acid (188.4 mg), triethylcitrate (10.4 mg), polysorbate 80 (3.8 mg), mannitol (88.4 mg) and carmellose sodium (25 mg). The prefilled syringe containing the clear reconstitution diluent (2 mL) contains mannitol (16 mg), water for injection, and sodium hydroxide and hydrochloric acid to control pH.

LUTRATE DEPOT is an extended release sterile, single dose injection in suspension form for intramuscular administration.

12 CLINICAL PHARMACOLOGY

12.1 Mechanism of Action

Leuprolide acetate, a GnRH agonist, acts as an inhibitor of gonadotropin secretion. Animal studies indicate that following an initial stimulation, continuous administration of leuprolide acetate results in suppression of ovarian and testicular steroidogenesis. This effect was reversible upon discontinuation of drug therapy.

Administration of leuprolide acetate has resulted in inhibition of the growth of certain hormone dependent tumors (prostate tumors in Noble and Dunning male rats and DMBA-induced mammary tumors in female rats) as well as atrophy of the reproductive organs.

12.2 Pharmacodynamics

In humans, administration of leuprolide acetate results in an initial increase in circulating levels of luteinizing hormone (LH) and follicle stimulating hormone (FSH), leading to a transient increase in levels of the gonadal steroids (testosterone and dihydrotestosterone in males, and estrone and estradiol in premenopausal females). However, continuous administration of leuprolide acetate results in decreased levels of LH and FSH. In males, testosterone is reduced to below castrate threshold. In premenopausal females, estrogens are reduced to postmenopausal concentrations. These decreases occur within two to four weeks after initiation of treatment. Long-term studies have shown that continuation of therapy with leuprolide acetate maintains testosterone below the castrate level for more than five years.

Leuprolide acetate is not active when given orally.

12.3 Pharmacokinetics

Absorption

Following two sequential injections of LUTRATE DEPOT 22.5 mg administered with a 3-month interval, plasma leuprolide acetate concentrations were similar among both cycles. After first administration, mean plasma leuprolide concentration of 46.8 ng/mL was observed at approximately 2 hours and the mean concentration then declined until next injection.

Distribution

The mean steady-state volume of distribution of leuprolide acetate following intravenous bolus administration to healthy male volunteers was 27 L. In vitro binding to human plasma proteins ranged from 43% to 49%.

Elimination

The mean systemic clearance of leuprolide acetate following intravenous bolus administration to healthy male volunteers was 7.6 L/h, and terminal elimination half-life was approximately 3 hours based on a two-compartment model.

Upon administration with different leuprolide acetate formulations, the major metabolite of leuprolide acetate is a pentapeptide (M- 1) metabolite.

13 NONCLINICAL TOXICOLOGY

13.1 Carcinogenesis, Mutagenesis, Impairment of Fertility

Two-year carcinogenicity studies were conducted with leuprolide acetate in rats and mice. In rats, a dose-related increase of benign pituitary hyperplasia and benign pituitary adenomas was noted at 24 months when the drug was administered subcutaneously at high daily doses (0.6 to 4 mg/kg). There was a significant but not dose-related increase of pancreatic islet cell adenomas in females and of testicular interstitial cell adenomas in males (highest incidence in the low dose group). In mice, no leuprolide acetate-induced tumors or pituitary abnormalities were observed at a dose as high as 60 mg/kg for two years. Patients have been treated with leuprolide acetate for up to three years with doses as high as 10 mg/day and for two years with doses as high as 20 mg/day without demonstrable pituitary abnormalities. No carcinogenicity studies have been conducted with LUTRATE DEPOT.

Genotoxicity studies were conducted with leuprolide acetate using bacterial and mammalian systems. These studies provided no evidence of mutagenic effects or chromosomal aberrations.

Leuprolide acetate may reduce male and female fertility. Administration of leuprolide acetate to male and female rats at dose of 0.024, 0.24, and 2.4 mg/kg as monthly depot formulation for up to 3 months (approximately as low as 1/30 of the human dose based on body surface area using an estimated daily dose in animals and humans) caused atrophy of the reproductive organs, and suppression of reproductive function. These changes were reversible upon cessation of treatment.

14 CLINICAL STUDIES

14.1 LUTRATE DEPOT 22.5 mg for 3-Month Administration

The efficacy of LUTRATE DEPOT 22.5 mg was evaluated in an open-label, multicenter, non-controlled, multiple dose clinical trial which enrolled 162 evaluable patients with prostate cancer. Patients were administered LUTRATE DEPOT 22.5 mg intramuscularly in 2 doses (157 received 2 injections) with a 3-month interval.

The median age was 71 years (range; 47-91), 62% White, and 30% Black or African-American.

Castrate levels of serum testosterone (<50 ng/dL) were achieved and maintained from Day 28 to 168 in 94.3% (95% CI:89.4, 97.0) of patients. On Day 28, 160 of the 162 (98.8%) patients had castrate testosterone levels. One patient did not achieve a castrate level and one had a missing value. Testosterone escapes (any value > 50 ng/dL after castrate levels were achieved) occurred in four patients. In addition, three patients had a single unevaluable testosterone level after Day 28 that was considered to be non-castrate in this analysis.

Figure 1. Mean testosterone plasma levels during treatment with two three-month IM injections of LUTRATE DEPOT 22.5 mg

15 REFERENCES

1. “OSHA Hazardous Drugs.” OSHA. http://www.osha.gov/SLTC/hazardousdrugs/index.html

16 HOW SUPPLIED/STORAGE AND HANDLING

LUTRATE® DEPOT is supplied as a kit consisting of a LEUPROLIDE ACETATE MIXJECT single-dose delivery system consisting of a vial with a Flip-Off seal containing sterile, white to off white lyophilized leuprolide acetate microspheres incorporated in a biodegradable polymer, a MIXJECT vial adapter containing the needle, and a pre-filled syringe containing clear sterile mannitol solution for injection, USP, 2 mL, pH 4.5 to 7.0.

LUTRATE® DEPOT (leuprolide acetate for depot suspension) 22.5 mg – NDC 83831-134-01

Storage

Store at controlled room temperature at 20°-25°C (68°-77°F); excursions permitted between 15°C and 30°C (59°F and 86°F) [see USP Controlled Room Temperature].

17 PATIENT COUNSELING INFORMATION

Hypersensitivity

- Inform patients that if they have experienced hypersensitivity with other GnRH agonist drugs like LUTRATE DEPOT, LUTRATE DEPOT is contraindicated [see Contraindications (4)].

Tumor Flare

- Inform patients that LUTRATE DEPOT can cause tumor flare during the first weeks of treatment. Inform patients that the increase in testosterone can cause an increase in urinary symptoms or pain. Advise patients to contact their healthcare provider if ureteral obstruction, spinal cord compression, paralysis, or new or worsened symptoms occur after beginning LUTRATE DEPOT treatment [see Warnings and Precautions (5.1)].

Metabolic Syndrome

- Advise patients that there is an increased risk of metabolic changes such as hyperglycemia, diabetes, hyperlipidemia, and non-alcoholic fatty liver disease with LUTRATE DEPOT therapy. Inform patients that periodic monitoring for metabolic changes is required when being treated with LUTRATE DEPOT [see Warnings and Precautions (5.2)].

Cardiovascular Disease

- Inform patients that there is an increased risk of myocardial infarction, sudden cardiac death, and stroke with LUTRATE DEPOT treatment. Advise patients to immediately report signs and symptoms associated with these events to their healthcare provider for evaluation [see Warnings and Precautions (5.3)].

Severe Cutaneous Adverse Reactions

- Inform patients that severe cutaneous adverse reactions (SCARs), including Stevens-Johnson syndrome (SJS), toxic epidermal necrolysis (TEN), drug reaction with eosinophilia and systemic symptoms (DRESS), and acute generalized exanthematous pustulosis (AGEP), which may be life threating or fatal, may occur during treatment with LUTRATE DEPOT.
- Advice patients to contact their healthcare provider or seek medical attention right away if they experience signs or symptoms of SCARs [see Warnings and Precautions (5.6)].

Urogenital Disorders

- Advise patients that LUTRATE DEPOT may cause impotence [see Use In Specific Populations (8.3)].

Infertility

- Inform patients that LUTRATE DEPOT may cause infertility [see Use In Specific Populations (8.3)].

Continuation of LUTRATE DEPOT Treatment

- Inform patients that LUTRATE DEPOT is usually continued, often with additional medication, after the development of metastatic castration-resistant prostate cancer [see Dosage and Administration (2.1)].

Trademarks are property of their respective owners and are not of Avyxa Pharma, LLC

For more information or a video demonstration on how to use, scan the code below or call 1-888-520-0954.

Manufactured for:
Avyxa Pharma, LLC
New Jersey 07054, USA
Made in Spain
99356473

PACKAGE LABEL

NDC 83831-134-01 Rx Only

Lutrate® Depot
(Leuprolide acetate for depot suspension)

22.5 mg

For intramuscular injection

See package insert for reconstitution and administration procedures
Recommended dose: one intramuscular injection every three months

Sterile
Must be reconstituted before use

AVYXA